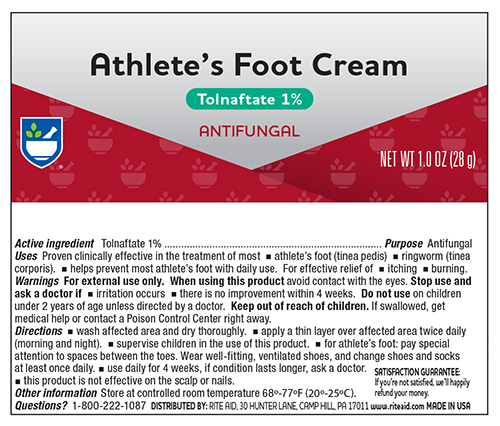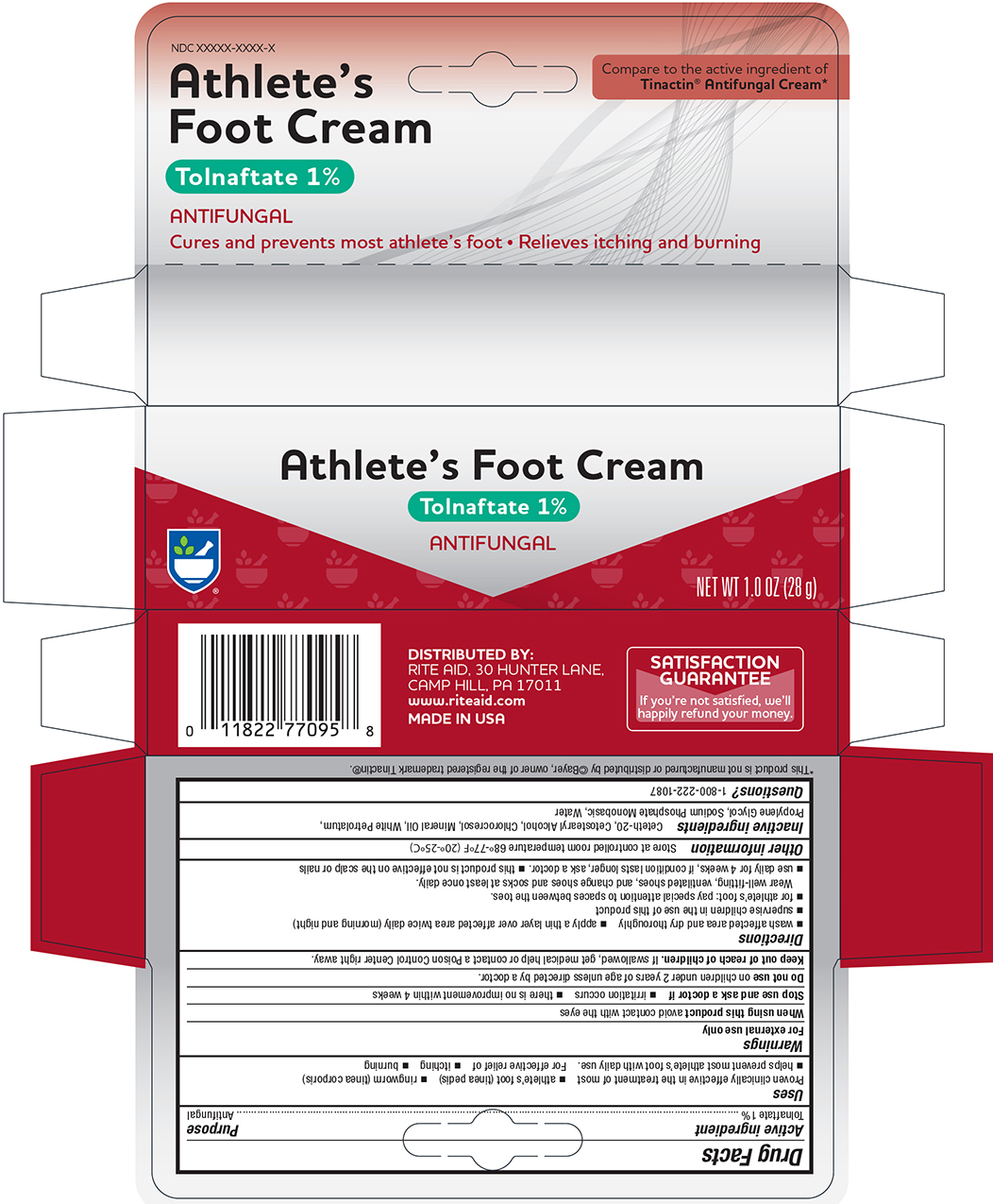 DRUG LABEL: Rite Aid Athletes Foot
NDC: 11822-0051 | Form: CREAM
Manufacturer: RITE AID
Category: otc | Type: HUMAN OTC DRUG LABEL
Date: 20241121

ACTIVE INGREDIENTS: TOLNAFTATE 10 mg/1 g
INACTIVE INGREDIENTS: WATER; CETOSTEARYL ALCOHOL; CETETH-20; CHLOROCRESOL; MINERAL OIL; PETROLATUM; SODIUM PHOSPHATE, MONOBASIC, ANHYDROUS; PROPYLENE GLYCOL

Rite Aid Athletes Foot

Drug Facts

Active ingredient

Tolnaftate USP 1%

Purpose

Antifungal

Uses

- for effective treatment of most athlete's foot (tinea pedis), jock itch (tinea cruris) and ringworm (tinea corporis)
- for effective relief of itchy, scaly skin between the toes
- clears up most athlete's foot infection and with daily use helps keep it from coming back

Warnings

For external use only

Do not use

- on children under 2 years of age unless directed by a doctor

When using this product avoid contact with eyes

Stop use and ask a doctor if

- irritation occurs or if there is no improvement within 4 weeks (for athlete's foot and ringworm)
- irritation occurs or if there is no improvement within 2 weeks (for jock itch)

Keep this and all drugs out of the reach of children.

In case of accidental ingestion, seek professional assistance or contact a Poison Control Center immediately.

Directions

- clean the affected area and dry thoroughly
- apply a thin layer of the product over the affected area twice daily (morning and night) or as directed by a doctor
- supervise children in the use of this product

For athlete's foot

- use daily for 4 weeks. If condition persists longer, consult a doctor
- pay special attention to the spaces between the toes
- wear well fitting ventilated shoes
- change shoes and socks at least once daily

For ringworm, use daily for 4 weeks. If condition persists longer, consult a doctor.

For jock itch, use daily for 2 weeks. If condition persists longer, consult a doctor.

This product is not effective on the scalp or nails.

Other information

- Store at controlled room temperature 20°-25°C (68°-77°F)
- close cap tightly after use

Inactive ingredients

Ceteth-20, Cetostearyl Alcohol, Chlorocresol, Mineral Oil, Propylene Glycol, Purified Water, Sodium Phosphate Monobasic, White Petrolatum

Questions?

<For questions or comments or ot reprot an undesired reaction or side effect, please call >

Principal Display Panel – Tube

RITE AID Athleetes Foot *Compare to Active Ingredient of Tinactin®

NDC 11822-0051-1

Antifungal

Cream (Tolnaftate 1%)

CURES and PREVENTS Most ATHLETE'S FOOT,

Relives Burning, Itching and cracking Net Wt. 1.0 OZ (28 g)

Principal Display Panel – Carton

RITE AID Athlete's Foot NDC 11822-0051-1

Antifungal *Compare to Active Ingredient of Tinactin®

Cream (Tolnaftate 1%)

Cures and Prevents Most Athlete's Foot

relieves burning ,itching,& cracking

Net Wt. 1.0 OZ (28 g)